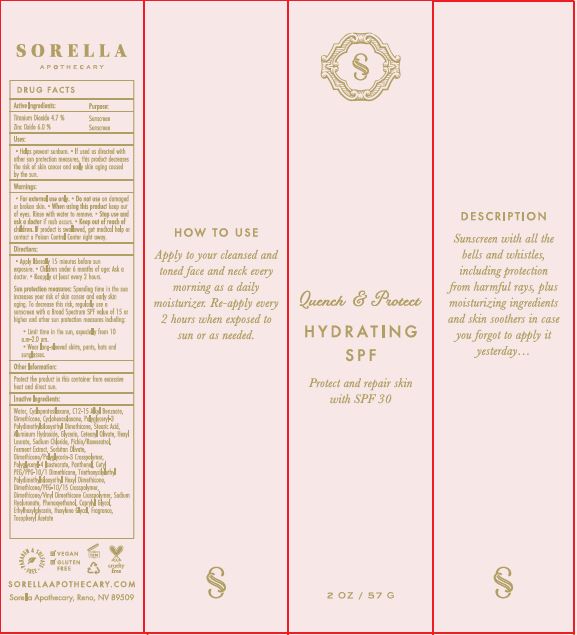 DRUG LABEL: Quench and Protect Hydrating SPF 30
NDC: 62742-4158 | Form: CREAM
Manufacturer: Allure Labs Inc
Category: otc | Type: HUMAN OTC DRUG LABEL
Date: 20171212

ACTIVE INGREDIENTS: ZINC OXIDE 60 mg/1 g; TITANIUM DIOXIDE 47 mg/1 g
INACTIVE INGREDIENTS: WATER; DIMETHICONE CROSSPOLYMER (450000 MPA.S AT 12% IN CYCLOPENTASILOXANE); C12-15 ALKYL ETHYLHEXANOATE; DIMETHICONE; STEARIC ACID; ALUMINUM HYDROXIDE; GLYCERIN; CETEARYL OLIVATE; POLYGLYCERYL-4 ISOSTEARATE; CETYL PEG/PPG-10/1 DIMETHICONE (HLB 4); HEXYL LAURATE; SODIUM CHLORIDE; PICHIA JADINII; SORBITAN OLIVATE; PANTHENOL; PEG-12 DIMETHICONE/PPG-20 CROSSPOLYMER; CAPRYLYL GLYCOL; PHENOXYETHANOL ; ETHYLHEXYLGLYCERIN; HEXYLENE GLYCOL; HYALURONATE SODIUM; TOCOPHERYL NICOTINATE, D-.ALPHA.

DRUG FACTS

ACTIVE INGREDIENTS:
Zinc Oxide - 6.0%
Titanium Dioxide 4.7%

Purpose: Sunscreen

INDICATIONS AND USAGE

How to use: Apply to your cleansed and toned face and neck every morning as a daily moisturizer. Re-apply every 2 hours when exposed to sun or as needed.

DOSAGE AND ADMINISTRATION

Apply to your cleansed and toned face and neck every morning as a daily moisturizer. Re-apply every 2 hours when exposed to sun or as needed.

INACTIVE INGREDIENT

Aqua, Cyclopentasiloxane, C12-15 Alkyl Benzoate, Dimethicone, Cyclohexasiloxane, Polyglyceryl-3 Polydimethylsiloxyethyl Dimethicone, Aluminum Hydroxide, Stearic Acid, Glycerin, Cetearyl Olivate,Hexyl Laurate, Sodium Chloride, Pichia/ Resveratrol, Ferment Extract, Sorbitane Olivate, Dimethicone/Polyglycerin -3 Crosspolymer, Polyglyceryl-4 Isostearate, Panthenol, Cetyl PEG/PPG-10/1 Dimethicone, Triethoxysilylethyl, Polydimethylsiloxyethyl Hexyl Dimethicone, Dimethicone/PEG-10/15 Crosspolymer, Dimethicone/Venyl Dimethicone, Crosspolymer, Sodium Hyaluronate, Phenoxyethanol, Caprylyl Glycol, , Ethylhexylglycerin, Hexylene Glycol, Fragrance, Tocopheryl Acetate.

PACKAGE LABEL

SORELLAAPOTHECARY.COM

Sorella Apothecary, Reno, NV 89509.